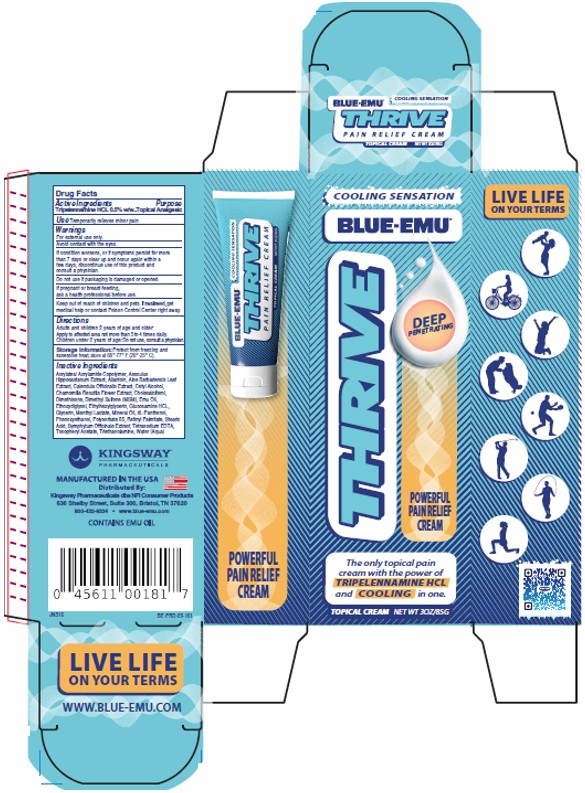 DRUG LABEL: Blue-Emu THRIVE Cooling
NDC: 69993-650 | Form: CREAM
Manufacturer: Kingsway Pharmaceuticals dba NFI, LLC
Category: otc | Type: HUMAN OTC DRUG LABEL
Date: 20251222

ACTIVE INGREDIENTS: TRIPELENNAMINE 0.5 g/100 g
INACTIVE INGREDIENTS: HORSE CHESTNUT; ALLANTOIN; ALOE VERA LEAF; CALENDULA OFFICINALIS FLOWERING TOP; CETYL ALCOHOL; CHAMOMILE; CHOLECALCIFEROL; DIMETHICONE, UNSPECIFIED; DIMETHYL SULFONE; EMU OIL; DIETHYLENE GLYCOL MONOETHYL ETHER; ETHYLHEXYLGLYCERIN; GLUCOSAMINE HYDROCHLORIDE; GLYCERIN; GLYCERYL MONOSTEARATE; MINERAL OIL; PANTHENOL; PHENOXYETHANOL; POLYSORBATE 85; VITAMIN A PALMITATE; STEARIC ACID; COMFREY ROOT; EDETATE SODIUM; .ALPHA.-TOCOPHEROL ACETATE; TROLAMINE; WATER

BLUE-EMU® THRIVE COOLING

Active Ingredients

Tripelennamine HCL 0.5% w/w

Purpose

Topical Analgesic

Use

Temporarily relieves minor pain

Warnings:

For external use only.
Avoid contact with the eyes.
If condition worsens, or if symptoms persist for more than 7 days or clear up and occur again within a few days, discontinue use of this product and consult a physician.

Do not use

if packaging is damaged or opened.

If pregnant or breast-feeding,

ask a health professional before use.

Keep out of reach of children and pets.

If swallowed, get medical help or contact Poison Control Center right away.

Directions

Adults and children 2 years of age and older:
Apply to affected area not more than 3 to 4 times daily.
Children under 2 years of age: Do not use, consult a physician.

Storage Information:

Protect from freezing and excessive heat, store at 68°-77°F (20°-25°C).

Inactive Ingredients

Acrylates/ Acrylamide Copolymer, Aesculus Hippocastanum Extract, Allantoin, Aloe Barbadensis Leaf Extract, Calendula Officinalis Extract, Cetyl Alcohol, Chamomilla Recutita Flower Extract, Cholecalciferol, Dimethicone, Dimethyl Sulfone (MSM), Emu Oil, Ethoxydiglycol, Ethylhexylglycerin, Glucosamine HCL, Glycerin, Menthyl Lactate, Mineral Oil, dL-Panthenol, Phenoxyethanol, Polysorbate 85, Retinyl Palmitate, Stearic Acid, Symphytum Officinale Extract, Tetrasodium EDTA, Tocopheryl Acetate, Triethanolamine, Water (Aqua)
KINGSWAY™
PHARMACEUTICALS
MANUFACTURED IN THE USA
Distributed By:
Kingsway Pharmaceuticals dba NFI Consumer Products
636 Shelby Street, Suite 300, Bristol, TN 37620
800-432-9334 • www.blue-emu.com
CONTAINS EMU OIL
LIVE LIFE
ON YOUR TERMS
WWW.BLUE-EMU.COM

PRINCIPAL DISPLAY PANEL – TUBE LABEL

LIVE LIFE
ON YOUR TERMS
COOLING SENSATION
BLUE-EMU®
THRIVE
DEEP
PENETRATING

POWERFUL
PAIN RELIEF
CREAM
The only topical pain
cream with the power of
TRIPELENNAMINE HCL
and COOLING in one.
TOPICAL CREAM NET WT 3OZ/85G